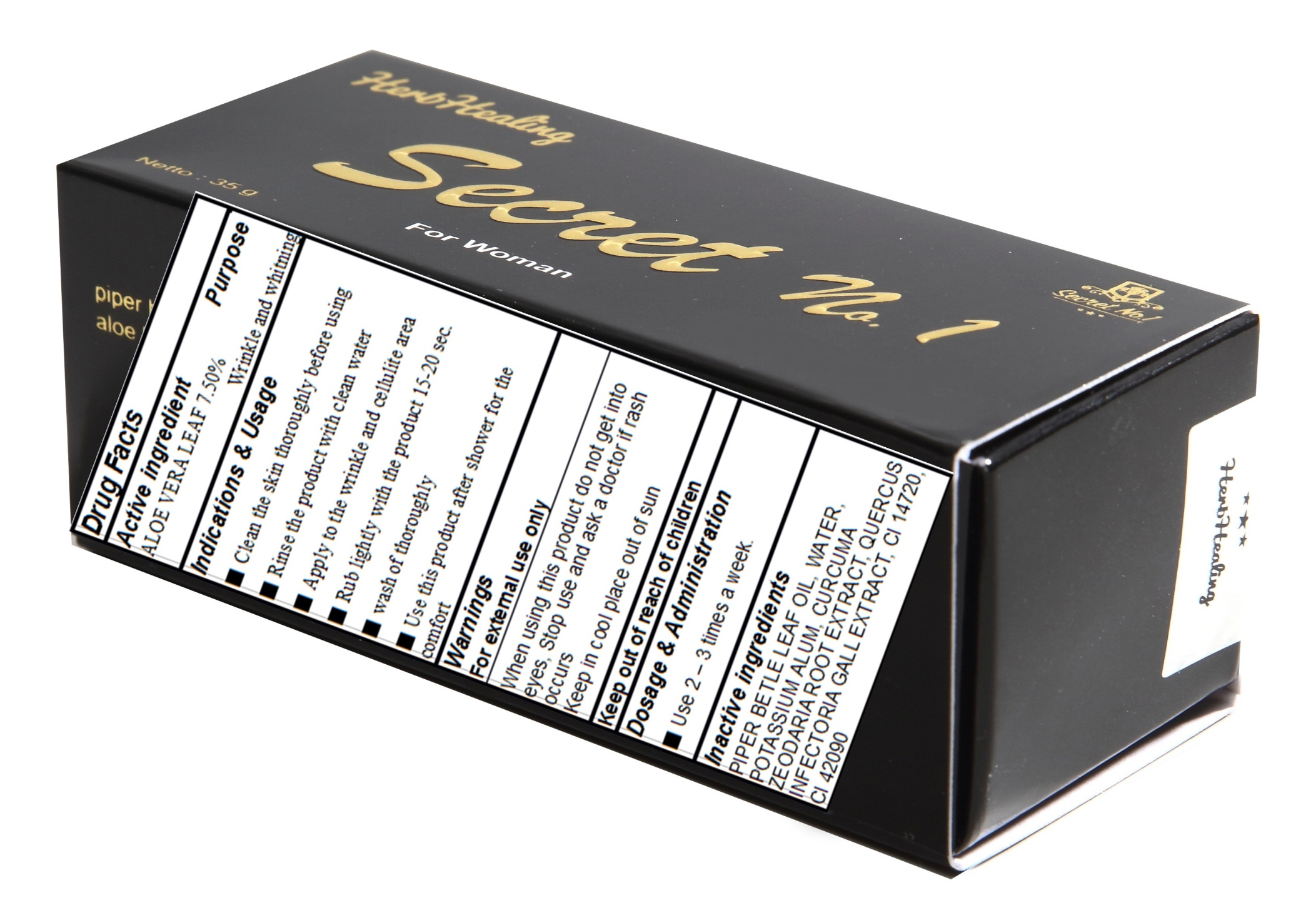 DRUG LABEL: Secret No 1
NDC: 70869-010 | Form: STICK
Manufacturer: KJ TRADING, JK GLOBAL(TRADE)
Category: otc | Type: HUMAN OTC DRUG LABEL
Date: 20160802

ACTIVE INGREDIENTS: ALOE VERA LEAF 2.62 g/35 g
INACTIVE INGREDIENTS: WATER

ACTIVE INGREDIENT

Active Ingredient: ALOE VERA LEAF 7.50%

INACTIVE INGREDIENT

Inactive Ingredients: PIPER BETLE LEAF OIL, WATER, POTASSIUM ALUM, CURCUMA ZEODARIA ROOT EXTRACT, QUERCUS INFECTORIA GALL EXTRACT, CI 14720, CI 42090

PURPOSE

Purpose: wrinkle and cellulite cares

WARNINGS

Warnings: For external use only When using this product do not get into eyes, Stop use and ask a doctor if rash occurs Keep out of reach of children Keep in cool place out of sun

KEEP OUT OF REACH OF CHILDREN

INDICATIONS & USAGE

Indications & usage: - Rinse the product with clean water - Clean the skin thoroughly before using - Apply to the wrinkle and cellulite area - Rub lightly with the stick 15-20 sec. - Wash off thoroughly - Use this product after shower for the comfort.

DOSAGE & ADMINISTRATION

Dosage & administration: - Use 2 – 3 times a week.